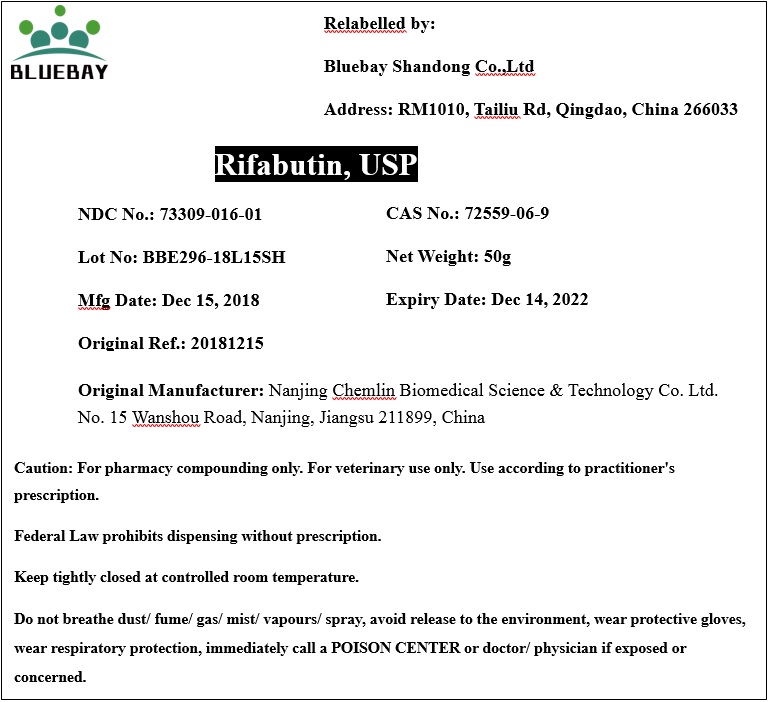 DRUG LABEL: Rifabutin
NDC: 73309-016 | Form: POWDER
Manufacturer: BLUEBAY SHANDONG CO.,LTD
Category: other | Type: BULK INGREDIENT
Date: 20190819

ACTIVE INGREDIENTS: RIFABUTIN 1 g/1 g

Rifabutin